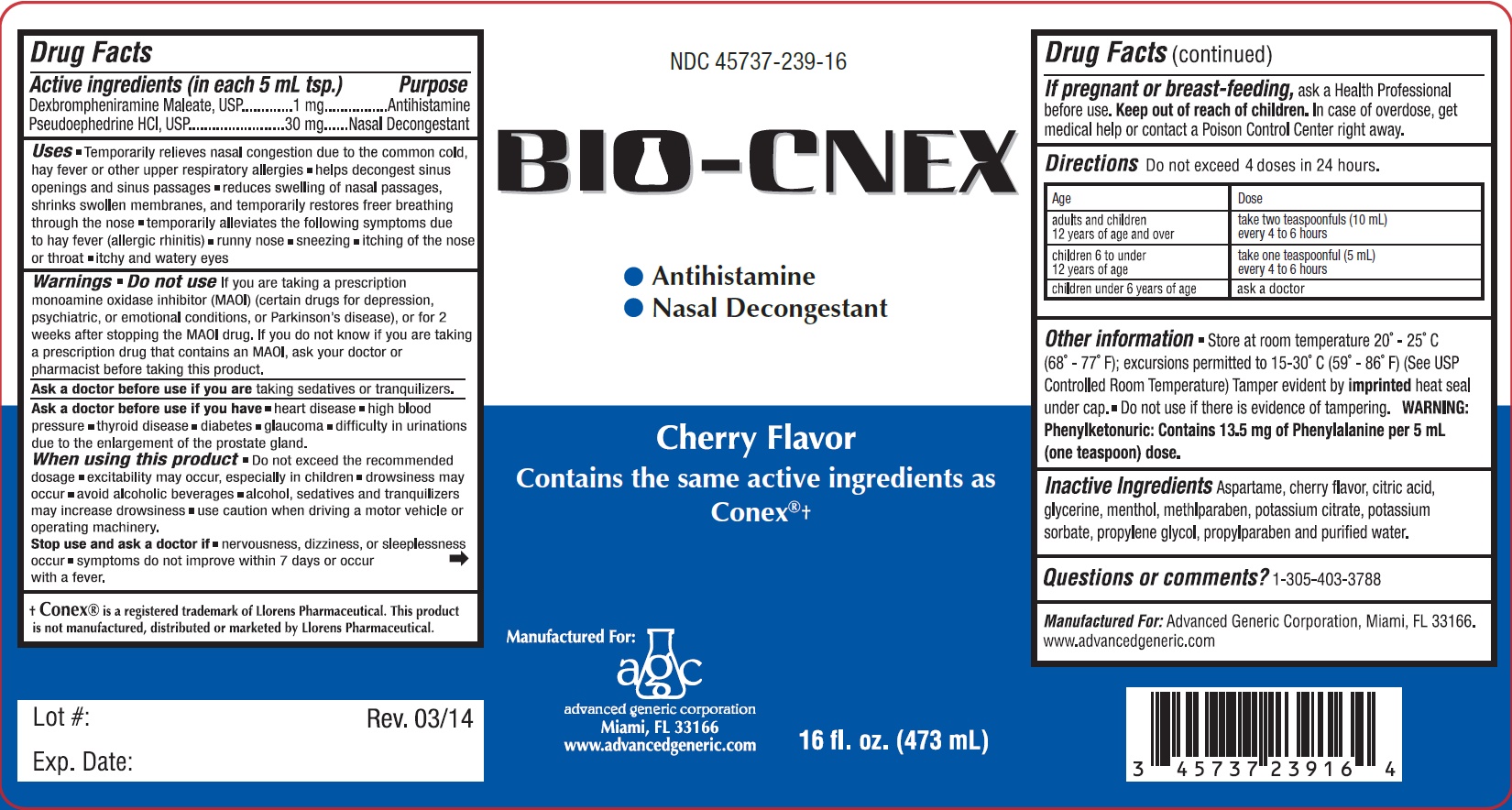 DRUG LABEL: BIO-CNEX
NDC: 45737-239 | Form: LIQUID
Manufacturer: Advanced Generic Corporation
Category: otc | Type: HUMAN OTC DRUG LABEL
Date: 20241220

ACTIVE INGREDIENTS: DEXBROMPHENIRAMINE MALEATE 1 mg/5 mL; PSEUDOEPHEDRINE HYDROCHLORIDE 30 mg/5 mL
INACTIVE INGREDIENTS: ASPARTAME; ANHYDROUS CITRIC ACID; GLYCERIN; MENTHOL; METHYLPARABEN; POTASSIUM CITRATE; POTASSIUM SORBATE; PROPYLENE GLYCOL; PROPYLPARABEN; WATER

AGC-BioCNex 239

Active ingredients (in each 5 mL tsp.) Purpose

Dexbrompheniramine maleate 1 mg Antihistamine

Pseudoephedrine Hydrochloride 30 mg Nasal Decongestant

Purpose

Antihistamine

Nasal Decongestant

Warnings

DO not use If you are taking a prescription monoamine oxidase inhibitor (MAOI) (certain drugs for depression, psychiatric, or emotional conditions, or Parkinson's disease), or for 2 weeks after stopping the MAOI drug. If you do not know if you are taking a prescription drug that contains an MAOI, ask your doctor or pharmacist before taking this product.

Ask a doctor before use if you are taking sedative or tranquilizers.

Ask a doctore before use if you have

- heart disease
- high blood pressure
- thyroid disease
- diabetes
- glaucoma
- difficulty in urinations due to the enlargment of the prostate gland.

When using this product

- Do not exceed the recommended dosage
- excitability may occur, espicially in children
- drowsiness may occur
- avoid alcoholic beverages
- alcohol, sedatives and tranquilizers may increase drowsiness
- use cuation when driving a motor vehicle or operating machinery.

Stop use and ask a doctor if

- nervousness, dizziness, or sleeplessness occur
- symptoms do not improve within 7 days or occur with fever.

Keep out of reach of children.In case of overdose, get medical help or contact a Poison Control Center right away

PREGNANCY OR BREAST FEEDING

If pregnant or breast-feeding,ask a Health Professional before use.

DOSAGE AND ADMINISTRATION

Directionsdo not exceed 4 doses in 24 hours.

adults and children 12 years of age and over | take two teaspoonfuls (10 mL); every 4 to 6 hours
children 6 to under 12 years of age | take one teaspoonful (5 mL); every 4 to 6 hours
children under 6 years of age | ask a doctor

Uses

- Temporarily relieves nasal congestion due to the common cold, hay fever or other upper respiratory allergies
- helps decongest sinus opening and sinus passages
- reduces swelling of nasal pasages, shrinks swollen membranes, and temporarily restores freer breathing through the nose
- temporarily alleviates the following symptoms due to hay fever (allergic rhinitis)
- runny nose
- sneezing
- itching of the nose or throat
- itchy and watery eyes

INACTIVE INGREDIENT

Inactive ingredients Aspertame, cherry flavor, citric acid, glycerine, menthol, methylparaben, potsassium citrate, potassium sorbate, propylene glycol, propylparaben and purified water.

Questions or comments?

1-305-403-3788